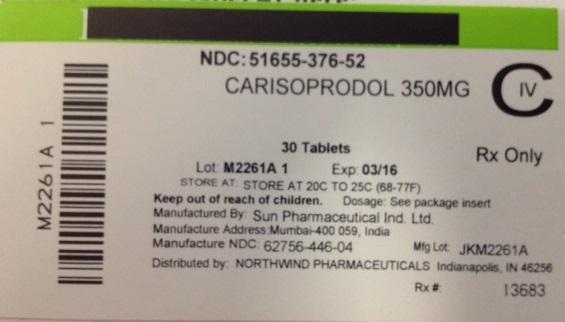 DRUG LABEL: Carisoprodol
NDC: 51655-376 | Form: TABLET
Manufacturer: Northwind Pharmaceuticals
Category: prescription | Type: HUMAN PRESCRIPTION DRUG LABEL
Date: 20140618

ACTIVE INGREDIENTS: CARISOPRODOL 350 mg/1 1

Indications and Usage

Carisoprodol is indicated for the relief of discomfort associated with acute, painful musculoskeletal conditions in adults.

Carisoprodol tablets, USP should only be used for short periods (up to two or three weeks) because adequate evidence of effectiveness for more prolonged use has not been established and because acute, painful musculoskeletal conditions are generally of short duration [see Dosage and Administration (2)].

Dosage and Administration

The recommended dose of carisoprodol is 350 mg three times a day and at bedtime. The recommended maximum duration of carisoprodol tablets use is up to two or three weeks.

Dosage Forms and Strengths

350 mg Tablets: round, convex, white tablets, inscribed with “446” on one side and plain on other side

Contraindications

Carisoprodol tablets are contraindicated in patients with a history of acute intermittent porphyria or a hypersensitivity reaction to a carbamate such as meprobamate.

Warnings and Precautions

5.1 Sedation

Carisoprodol has sedative properties (in the low back pain trials, 13% to 17% of patients who received carisoprodol experienced sedation compared to 6% of patients who received placebo) [see ADVERSE REACTIONS (6.1)] and may impair the mental and/or physical abilities required for the performance of potentially hazardous tasks such as driving a motor vehicle or operating machinery. There have been postmarketing reports of motor vehicle accidents associated with the use of carisoprodol.

Since the sedative effects of carisoprodol and other CNS depressants (e.g., alcohol, benzodiazepines, opioids, tricyclic antidepressants) may be additive, appropriate caution should be exercised with patients who take more than one of these CNS depressants simultaneously.5.2 Drug Dependence, Withdrawal, and Abuse

In the postmarketing experience with carisoprodol, cases of dependence, withdrawal, and abuse have been reported with prolonged use. Most cases of dependence, withdrawal, and abuse occurred in patients who have had a history of addiction or who used carisoprodol in combination with other drugs with abuse potential. However, there have been postmarketing adverse event reports of carisoprodol-associated abuse when used without other drugs with abuse potential. Withdrawal symptoms have been reported following abrupt cessation after prolonged use. To reduce the chance of carisoprodol dependence, withdrawal, or abuse, carisoprodol should be used with caution in addiction-prone patients and in patients taking other CNS depressants including alcohol, and carisoprodol should not be used more than two to three weeks for the relief of acute musculoskeletal discomfort.

Carisoprodol, and one of its metabolites, meprobamate (a controlled substance), may cause dependence [see Clinical Pharmacology (12.3)].

5.3 Seizures

There have been postmarketing reports of seizures in patients who received carisoprodol. Most of these cases have occurred in the setting of multiple drug overdoses (including drugs of abuse, illegal drugs, and alcohol) [see Overdosage (10)].

Adverse Reactions

6.1 Clinical Studies Experience

Because clinical studies are conducted under widely varying conditions, adverse reaction rates observed in clinical studies of a drug cannot be directly compared to rates in the clinical studies of another drug and may not reflect rates observed in practice.

The data described below are based on 839 patients pooled from a double blind, randomized, multicenter, placebo controlled, one-week trial in adult patients with acute, mechanical, lower back pain [see Clinical Studies (14)]. In the study, patients were treated with 350 mg of carisoprodol, or placebo three times a day and at bedtime for seven days. The mean age was about 41 years old with 54% females and 46% males and 74 % Caucasian, 16 % Black, 9% Asian, and 2% other.

There were no deaths and there were no serious adverse reactions in the trial. In the study, 2.7%, and 5.4%, of patients treated with placebo, and 350 mg of carisoprodol, respectively, discontinued due to adverse events; and 0.5%, and 1.8% of patients treated with placebo, and 350 mg of carisoprodol, respectively, discontinued due to central nervous system adverse reactions.

6.2 Postmarketing Experience

The following events have been reported during postapproval use of carisoprodol. Because these reactions are reported voluntarily from a population of uncertain size, it is not always possible to reliably estimate their frequency or establish a causal relationship to drug exposure.

Cardiovascular: Tachycardia, postural hypotension, and facial flushing [see Overdosage (10)].

Central Nervous System: Drowsiness, dizziness, vertigo, ataxia, tremor, agitation, irritability, headache, depressive reactions, syncope, insomnia, and seizures [see Overdosage (10)].

Gastrointestinal: Nausea, vomiting, and epigastric discomfort.

Hematologic: Leukopenia, pancytopenia

Drug Interactions

7.1 CNS Depressants

The sedative effects of carisoprodol and other CNS depressants (e.g., alcohol, benzodiazepines, opioids, tricyclic antidepressants) may be additive. Therefore, caution should be exercised with patients who take more than one of these CNS depressants simultaneously. Concomitant use of carisoprodol and meprobamate, a metabolite of carisoprodol, is not recommended [see Warnings and Precautions (5.1)].

7.2 CYP2C19 Inhibitors and Inducers

Carisoprodol is metabolized in the liver by CYP2C19 to form meprobamate [see Clinical Pharmacology (12.3)]. Coadministration of CYP2C19 inhibitors, such as omeprazole or fluvoxamine, with carisoprodol could result in increased exposure of carisoprodol and decreased exposure of meprobamate. Coadministration of CYP2C19 inducers, such as rifampin or St. John’s Wort, with carisoprodol could result in decreased exposure of carisoprodol and increased exposure of meprobamate. Low dose aspirin also showed an induction effect on CYP2C19. The full pharmacological impact of these potential alterations of exposures in terms of either efficacy or safety of carisoprodol is unknown.

Use in specific populations

8.1 Pregnancy: Pregnancy Category C.

There are no data on the use of carisoprodol during human pregnancy. Animal studies indicate that carisoprodol crosses the placenta and results in adverse effects on fetal growth and postnatal survival. The primary metabolite of carisoprodol, meprobamate, is an approved anxiolytic. Retrospective, postmarketing studies do not show a consistent association between maternal use of meprobamate and an increased risk for particular congenital malformations.

Teratogenic effects: Animal studies have not adequately evaluated the teratogenic effects of carisoprodol. There was no increase in the incidence of congenital malformations noted in reproductive studies in rats, rabbits, and mice treated with meprobamate. Retrospective, postmarketing studies of meprobamate during human pregnancy were equivocal for demonstrating an increased risk of congenital malformations following first trimester exposure. Across studies that indicated an increased risk, the types of malformations were inconsistent.

Nonteratogenic effects: In animal studies, carisoprodol reduced fetal weights, postnatal weight gain, and postnatal survival at maternal doses equivalent to 1 to 1.5 times the human dose (based on a body surface area comparison). Rats exposed to meprobamate in-utero showed behavioral alterations that persisted into adulthood. For children exposed to meprobamate in-utero, one study found no adverse effects on mental or motor development or IQ scores. Carisoprodol should be used during pregnancy only if the potential benefit justifies the risk to the fetus.8.2 Labor and Delivery

There is no information about the effects of carisoprodol on the mother and the fetus during labor and delivery.

8.3 Nursing Mothers

Very limited data in humans show that carisoprodol is present in breast milk and may reach concentrations two to four times the maternal plasma concentrations. In one case report, a breast-fed infant received about 4 to 6% of the maternal daily dose through breast milk and experienced no adverse effects. However, milk production was inadequate and the baby was supplemented with formula. In lactation studies in mice, female pup survival and pup weight at weaning were decreased. This information suggests that maternal use of carisoprodol may lead to reduced or less effective infant feeding (due to sedation) and/or decreased milk production. Caution should be exercised when carisoprodol is administered to a nursing woman.

8.4 Pediatric Use

The efficacy, safety, and pharmacokinetics of carisoprodol in pediatric patients less than 16 years of age have not been established.

8.5 Geriatric Use

The efficacy, safety, and pharmacokinetics of carisoprodol in patients over 65 years old have not been established.

8.6 Renal Impairment

The safety and pharmacokinetics of carisoprodol in patients with renal impairment have not been evaluated. Since carisoprodol is excreted by the kidney, caution should be exercised if carisoprodol is administered to patients with impaired renal function. Carisoprodol is dialyzable by hemodialysis and peritoneal dialysis.

8.7 Hepatic Impairment

The safety and pharmacokinetics of carisoprodol in patients with hepatic impairment have not been evaluated. Since carisoprodol is metabolized in the liver, caution should be exercised if carisoprodol is administered to patients with impaired hepatic function.

8.8 Patients with Reduced CYP2C19 Activity

Patients with reduced CYP2C19 activity have higher exposure to carisoprodol. Therefore, caution should be exercised in administration of carisoprodol to these patients [see Clinical Pharmacology (12.3)].

Drug abuse and dependence

Carisoprodol is not a controlled substance [see Warnings and Precautions (5.2)]. Discontinuation of carisoprodol in animals or in humans after chronic administration can produce withdrawal signs, and there are published case reports of human carisoprodol dependence.

In vitro studies demonstrate that carisoprodol elicits barbiturate-like effects. Animal behavioral studies indicate that carisoprodol produces rewarding effects. Monkeys self administer carisoprodol. Drug discrimination studies using rats indicate that carisoprodol has positive reinforcing and discriminative effects similar to barbital, meprobamate, and chlordiazepoxide.

Overdosage

Overdosage of carisoprodol commonly produces CNS depression. Death, coma, respiratory depression, hypotension, seizures, delirium, hallucinations, dystonic reactions, nystagmus, blurred vision, mydriasis, euphoria, muscular incoordination, rigidity, and/or headache have been reported with carisoprodol overdosage. Many of the carisoprodol overdoses have occurred in the setting of multiple drug overdoses (including drugs of abuse, illegal drugs, and alcohol). The effects of an overdose of carisoprodol and other CNS depressants (e.g., alcohol, benzodiazepines, opioids, tricyclic antidepressants) can be additive even when one of the drugs has been taken in the recommended dosage. Fatal accidental and non-accidental overdoses of carisoprodol have been reported alone or in combination with CNS depressants.

Treatment of Overdosage: Basic life support measures should be instituted as dictated by the clinical presentation of the carisoprodol overdose. Induced emesis is not recommended due to the risk of CNS and respiratory depression, which may increase the risk of aspiration pneumonia. Gastric lavage should be considered soon after ingestion (within one hour). Circulatory support should be administered with volume infusion and vasopressor agents if needed. Seizures should be treated with intravenous benzodiazepines and the reoccurrence of seizures may be treated with phenobarbital. In cases of severe CNS depression, airway protective reflexes may be compromised and tracheal intubation should be considered for airway protection and respiratory support.

The following types of treatment have been used successfully with an overdose of meprobamate, a metabolite of carisoprodol: activated charcoal (oral or via nasogastric tube), forced diuresis, peritoneal dialysis, and hemodialysis (carisoprodol is also dialyzable). Careful monitoring of urinary output is necessary and overhydration should be avoided. Observe for possible relapse due to incomplete gastric emptying and delayed absorption. For more information on the management of an overdose of carisoprodol, contact a Poison Control Center.

Patient information

Patients should be advised to contact their physician if they experience any adverse reactions to carisoprodol tablets.17.1 Sedation

Patients should be advised that carisoprodol tablets may cause drowsiness and/or dizziness, and has been associated with motor vehicle accidents. Patients should be advised to avoid taking carisoprodol tablets before engaging in potentially hazardous activities such as driving a motor vehicle or operating machinery [see Warnings and Precautions (5.1)].

17.2 Avoidance of Alcohol and Other CNS Depressants

Patients should be advised to avoid alcoholic beverages while taking carisoprodol tablets and to check with their doctor before taking other CNS depressants such as benzodiazepines, opioids, tricyclic antidepressants, sedating antihistamines, or other sedatives [see Warnings and Precautions (5.1)].

17.3 Carisoprodol Tablets Should Only Be Used for Short-Term Treatment

Patients should be advised that treatment with carisoprodol tablets should be limited to acute use (up to two or three weeks) for the relief of acute, musculoskeletal discomfort. In the postmarketing experience with carisoprodol tablets, cases of dependence, withdrawal, and abuse have been reported with prolonged use. If the musculoskeletal symptoms still persist, patients should contact their healthcare provider for further evaluation.

To report SUSPECTED ADVERSE REACTIONS, contact CARACO Pharmaceutical Laboratories Ltd. at 1-800-818-4555 or FDA at 1-800-FDA-1088 or www.fda.gov/medwatch.

For the manufacturer's complete drug information please visit the FDA:

http://dailymed.nlm.nih.gov/dailymed/lookup.cfm?setid=79ee419f-59ce-495b-8ec9-d1c6bb070d91

Label Display

NDC: 51655-376-52

Carisoprodol 350MG C IV

30 Tablets

Lot: Exp: Rx Only

Store at 20C to 25C (68-77F)

Keep out of reach of children. Dosage: See package insert

Manufactured by Sun Pharmaceuticals India Ltd

Manufacture address: Mumbai 400 059 India

Manufacture NDC: 62756-446-04 Mfg Lot:

Distributed by: Northwind Pharmaceutials Indianapolis, IN 46256